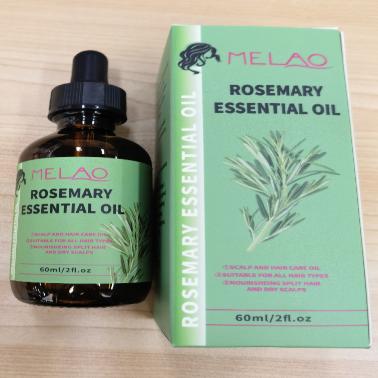 DRUG LABEL: MELAO ROSEMARY ESSENTIAL Oil
NDC: 83566-585 | Form: LIQUID
Manufacturer: Guangzhou Yilong Cosmetics Co., Ltd
Category: otc | Type: HUMAN OTC DRUG LABEL
Date: 20240827

ACTIVE INGREDIENTS: EUCALYPTOL 2.4 g/100 g
INACTIVE INGREDIENTS: MELALEUCA ALTERNIFOLIA (TEA TREE) LEAF OIL 2.3 g/100 g; (3,4-CYCLOHEXENYL)TRICHLOROSILANE 15 g/100 g; AGLAIA ODORATA FLOWER OIL 5 g/100 g; ROSMARINUS OFFICINALIS WHOLE 3.6 g/100 g; COTTONSEED OIL 26 g/100 g; DIMETHICONOL (40 CST) 9 g/100 g; TRIS-BHT MESITYLENE 4 g/100 g; PENTAMETHYL CYCLOPENTASILOXANE 29 g/100 g

MELAO ROSEMARY ESSENTIAL OIL

Active ingredients

Eucalyptol 2.40%

Inactive ingredients

Cyclopentasiloxane 29%

Dimethiconol 9%

Vitis Vinifera (Grape) Seed Oil 26%

Cyclohexasiloxane 15%

Rosa Rugosa Flower Oil 5%

BHT 4%

Lavandula Angustifolia(Lavender) Oil 3.70%

Rosmarinus Officinalis (Rosemary) Leaf Oil 3.60%

Melaleuca Alternifolia (Tea Tree)Leaf Oil 2.30%

Purpose

Moisture

-Uses

Step 1: Clean and thoroughly dry your hair.

Step 2: Rotate the bottle cap to open the product.

Step 3: Gently apply to the surface of the hair.

Warning

For external use only.

Stop use and ask a doctor if

.rash occurs.

Do not use

on damaged or broken skin.

When using this product

keep out of eyes. Rinse withwater to remove.

keep out of eyes. Rinse withwater to remove.

If swallowed, get medical help or contact a Poison Control Center right away.

DOSAGE & ADMINISTRATION

Squeeze out an appropriate amount of sunscreen and spread evenly on skin.